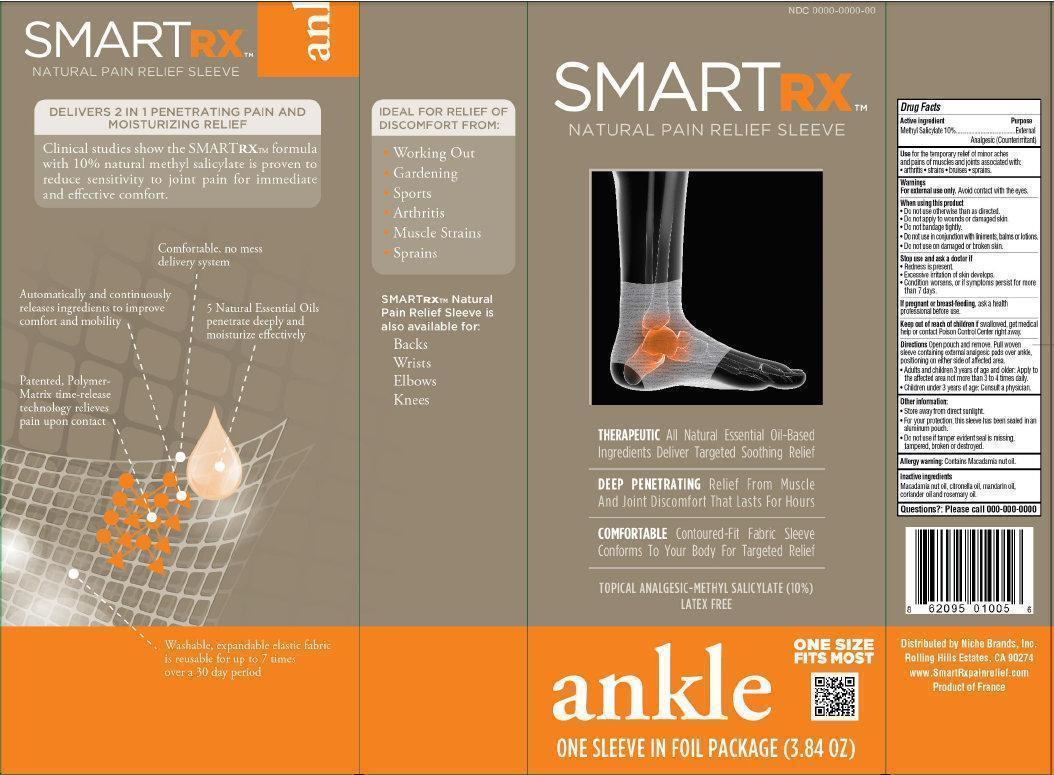 DRUG LABEL: SmartRx Natural Pain Relief Sleeve ANKLE
NDC: 60589-001 | Form: LIQUID
Manufacturer: Niche Brands, Inc.
Category: otc | Type: HUMAN OTC DRUG LABEL
Date: 20131227

ACTIVE INGREDIENTS: METHYL SALICYLATE 10 g/100 g
INACTIVE INGREDIENTS: MACADAMIA OIL; CITRONELLA OIL; MANDARIN OIL; CORIANDER OIL; ROSEMARY OIL

SmartRx Natural Pain Relief Sleeve ANKLE

Active ingredient

Methyl Salicylate 10%

Purpose

External Analgesic (Counterirritant)

Use

for the temporary relief of minor aches and pains of muscles and joints associated with • arthritis • strains • bruises • sprains.

Warnings

For external use only. Avoid contact with the eyes.

When using this product

- Do not use otherwise than as directed.
- Do not apply to wounds or damaged skin.
- Do not bandage tightly.
- Do not use in conjunction with liniments, balms or lotions.
- Do not use on damaged or broken skin.

Stop use and ask a doctor if

- Redness is present.
- Excessive irritation of skin develops.
- Condition worsens, or if symptoms persist for more than 7 days.

If pregnant or breast-feeding,

ask a health professional before use.

Keep out of reach of children

if swallowed, get medical help or contact Poison Control Center right away.

Directions

Open pouch and remove. Pull woven sleeve containing external analgesic pads over ankle, positioning on either side of affected area.

- Adults and children 3 years of age and older: Apply to the affected area not more than 3 to 4 times daily.
- Children under 3 years of age: Consult a physician.

Other information:

- Store away from direct sunlight.
- For your protection, this sleeve has been sealed in an aluminum pouch.
- Do not use if tamper evident seal is missing, tampered, broken or destroyed.

Allergy warning:

Contains Macadamia nut oil.

Inactive ingredients

Macadamia nut oil, citronella oil, mandarin oil, coriander oil and rosemary oil.

Questions?:

000-000-0000